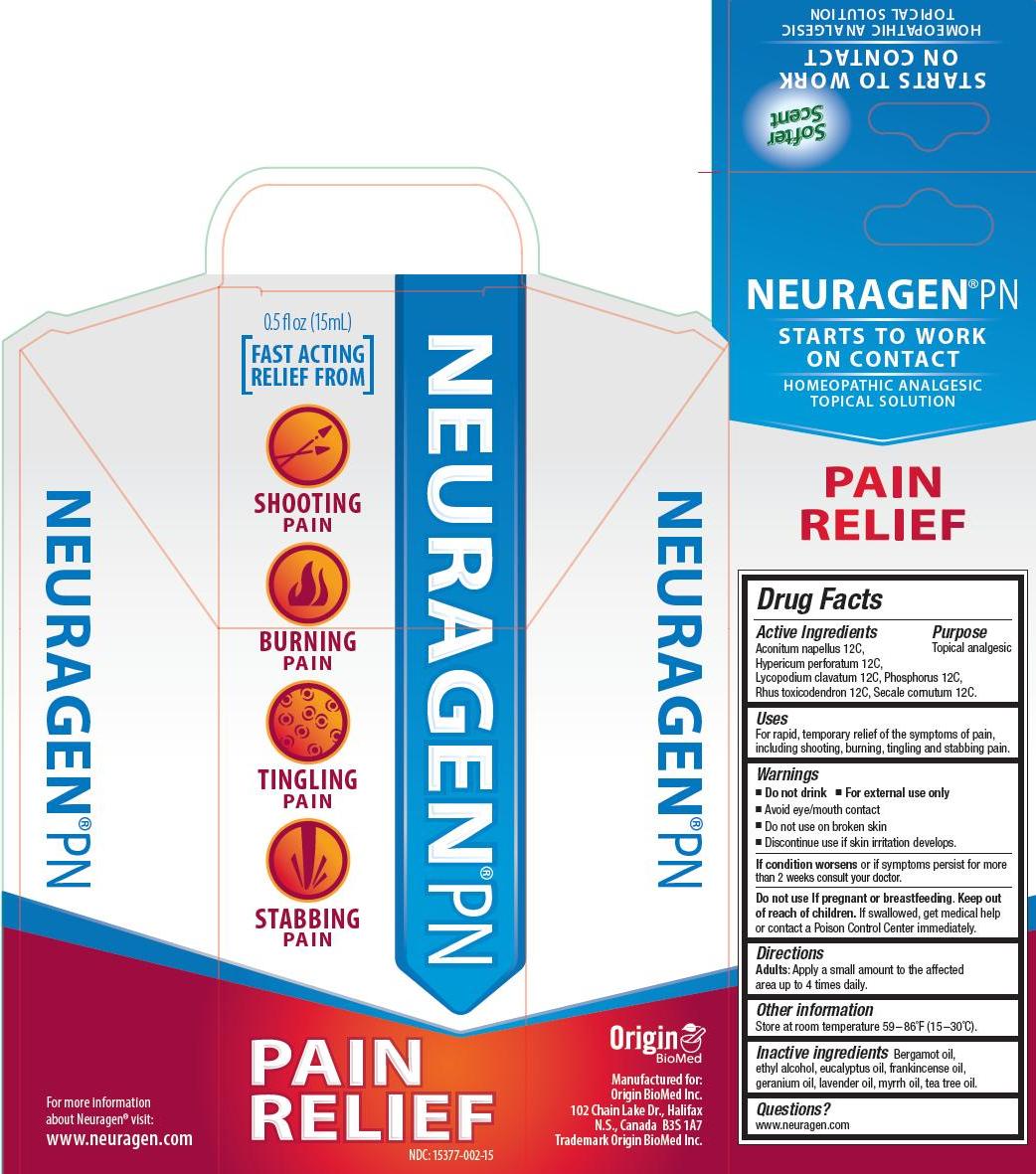 DRUG LABEL: Neuragen PN
                        
NDC: 15377-002 | Form: SOLUTION
Manufacturer: Origin Biomed Inc
Category: homeopathic | Type: HUMAN OTC DRUG LABEL
Date: 20140922

ACTIVE INGREDIENTS: HYPERICUM PERFORATUM 12 [hp_C]/15 mL; ACONITUM NAPELLUS 12 [hp_C]/15 mL; LYCOPODIUM CLAVATUM SPORE 12 [hp_C]/15 mL; PHOSPHORUS 12 [hp_C]/15 mL; TOXICODENDRON PUBESCENS LEAF 12 [hp_C]/15 mL; CLAVICEPS PURPUREA SCLEROTIUM 12 [hp_C]/15 mL
INACTIVE INGREDIENTS: BERGAMOT OIL; ALCOHOL; EUCALYPTUS OIL; GERANIUM OIL, ALGERIAN TYPE; LAVENDER OIL; TEA TREE OIL; FRANKINCENSE OIL; MYRRH OIL

Drug Facts

Active Ingredients

Aconitum napellus 12C, Hypericum perforatum 12C, Lycopodium clavatum 12C, Phosphorus 12C, Rhus toxicodendron 12C, Secale cornutum 12C

Purpose

Topical analgesic

Uses

For rapid, temporary relief of the symptoms of pain, including shooting, burning, tingling and stabbing pain.

Warnings

- Do not drink
- For external use only
- Avoid eye/mouth contact
- Strong floral aroma
- Do not use on broken skin
- Discontinue use if skin irritation develops

ASK DOCTOR

If condition worsens or if symptoms persist for more than 2 weeks consult your doctor.

Do not use if pregnant or breastfeeding.

Keep out of reach of children. If swallowed, get medical help or contact a Poison Control Center immediately.

Directions

Adults: Apply a small amount to the affected area up to 4 times daily.

Other information

Store at room temperature 59-86 degrees F (15-30 degrees C)

Inactive ingredients

bergamot oil, ethyl alcohol, eucalyptus oil, geranium oil, lavender oil, myrrh oil, tea tree oil

Questions?

www.neuragen.com

PACKAGE LABEL

0.5 fl. oz (15 ml)

[Fast acting relief from]

- shooting pain
- burning pain
- tingling pain
- stabbing pain

PAIN RELIEF